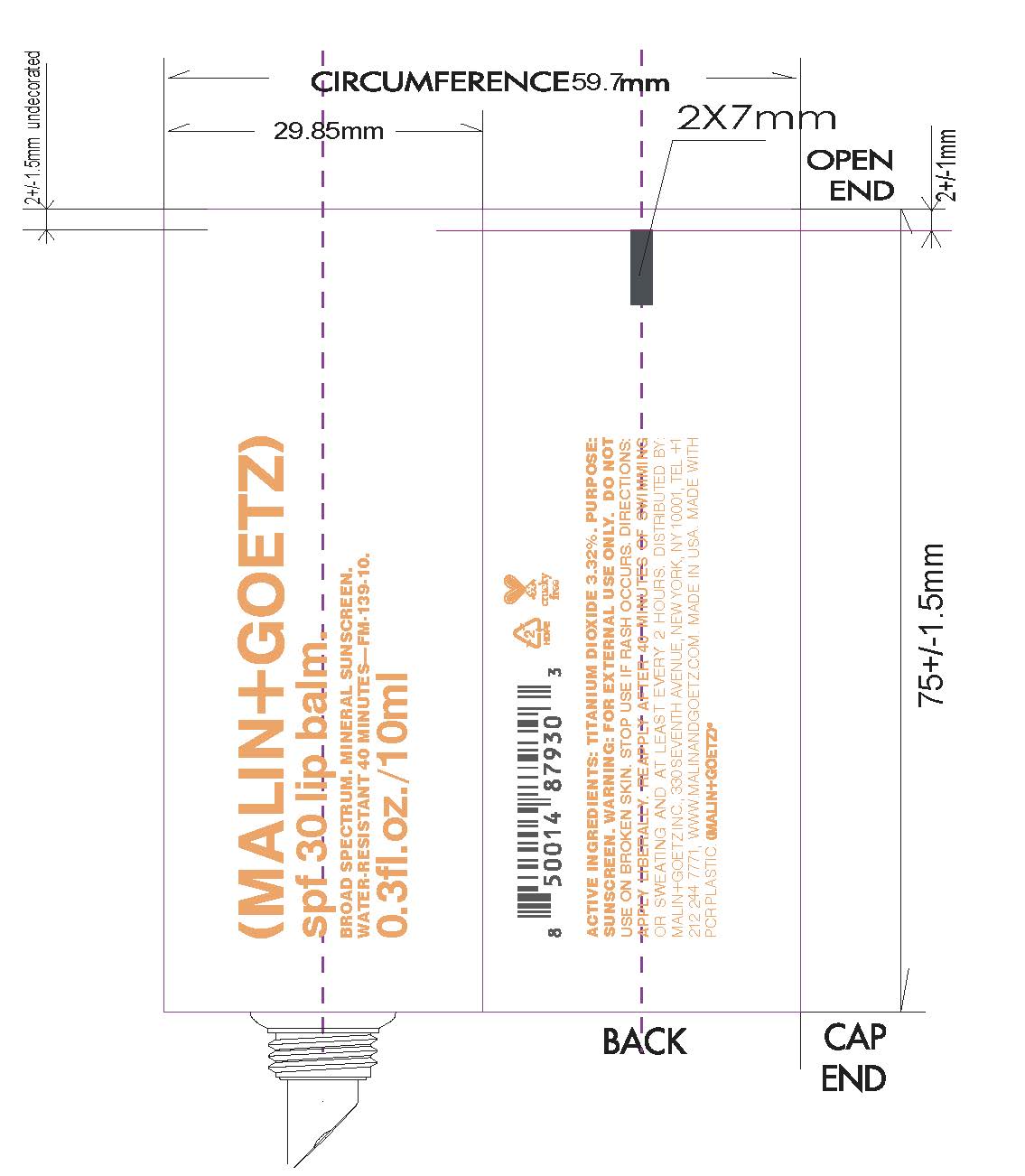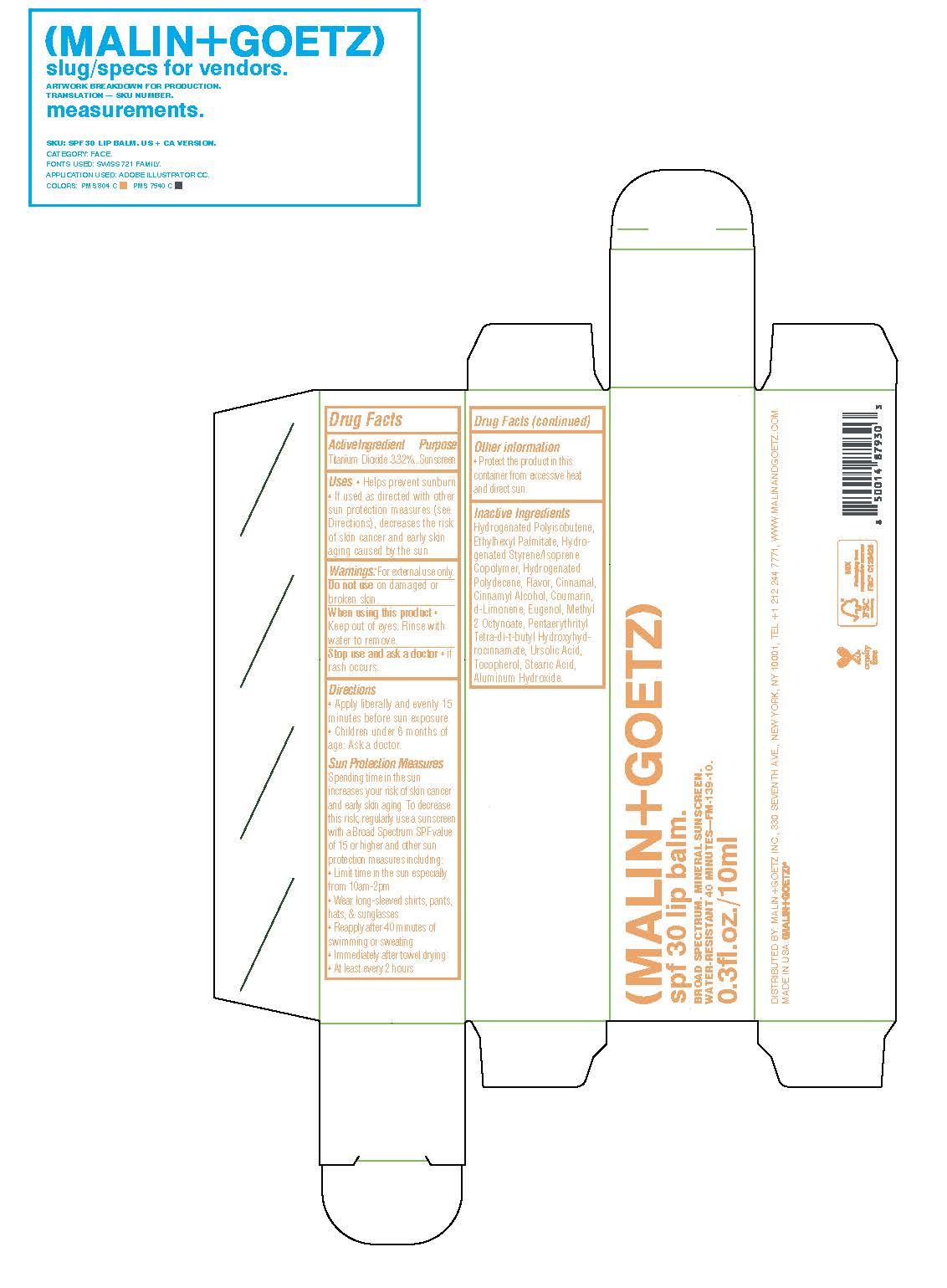 DRUG LABEL: spf 30 Lip Balm
NDC: 53634-129 | Form: STICK
Manufacturer: Malin and Goetz Inc
Category: otc | Type: HUMAN OTC DRUG LABEL
Date: 20251001

ACTIVE INGREDIENTS: TITANIUM DIOXIDE 3.3 g/100 mL
INACTIVE INGREDIENTS: EUGENOL; ALUMINUM HYDROXIDE; HYDROGENATED POLYDECENE TYPE I; LIMONENE, (+)-; METHYL HEPTINE CARBONATE; PENTAERYTHRITOL TETRAKIS(3-(3,5-DI-TERT-BUTYL-4-HYDROXYPHENYL)PROPIONATE); COUMARIN; TOCOPHEROL; URSOLIC ACID; CINNAMALDEHYDE; STEARIC ACID; CINNAMYL ALCOHOL; HYDROGENATED POLYBUTENE (1300 MW); ETHYLHEXYL PALMITATE

spf 30 Lip Balm

Active Ingredient Purpose

Titanium Dioxide 3.32% Sunscreen

Uses

- Helps prevent sunburn
- if used as directed with other sun protection measures (see Directions), decreases the risk of skin cancer and early skin aging caused by the sun

Keep out of reach of children. If swallowed, get medical help or contact a Poison Control Center right away

Stop use and ask a doctor

- If rash occurs

Warnings

For external use only

Do not use on damaged or broken skin

When using this product

- Keep out of eyes. Rinse with water to remove

Directions

- Apply Liberally and evenly 15 minutes before sun exposure
- Children under 6 months of age: Ask a doctor

Sun Protection Measures

Spending time in the sun increases your risk of skin cancer and early skin aging. To decrease this risk, regularly use a sunscreen with a Broad Spectrum SPF value of 15 or higher and other sun protection measures including:

- Limit time in the sun especially from 10 am- 2pm
- Wear long-sleeved shirts, pants, hats & sunglasses
- Reapply after 40 minutes of swimming or sweating
- Immediately after towel drying
- At least every 2 hours

Other information

- Protect the product in this container from excessive heat and direct sun

Inactive Ingredients

Hydrogenated Polyisobutene, Ethylhexyl Palmitate, Hydrogenated Styrene/Isoprene Copolymer, Hydrogenated Polydecene, Flavor, Cinnamal, Cinnamyl Alcohol, Coumarin, d-Limonene, Eugenol, Methyl 2 Octynoate, Pentaerythrityl Tetra-di-t-butyl Hydroxyhydrocinnamate, Urolic Acid, Tocopherol, Stearic Acid, Aluminum Hydroxide.

PACKAGE LABEL

(Malin+Goetz)

spf 30 lip balm.

Broad Spectrum Mineral Sunscreen

Water Resistant 40 minutes

0.3fl. oz./10ml